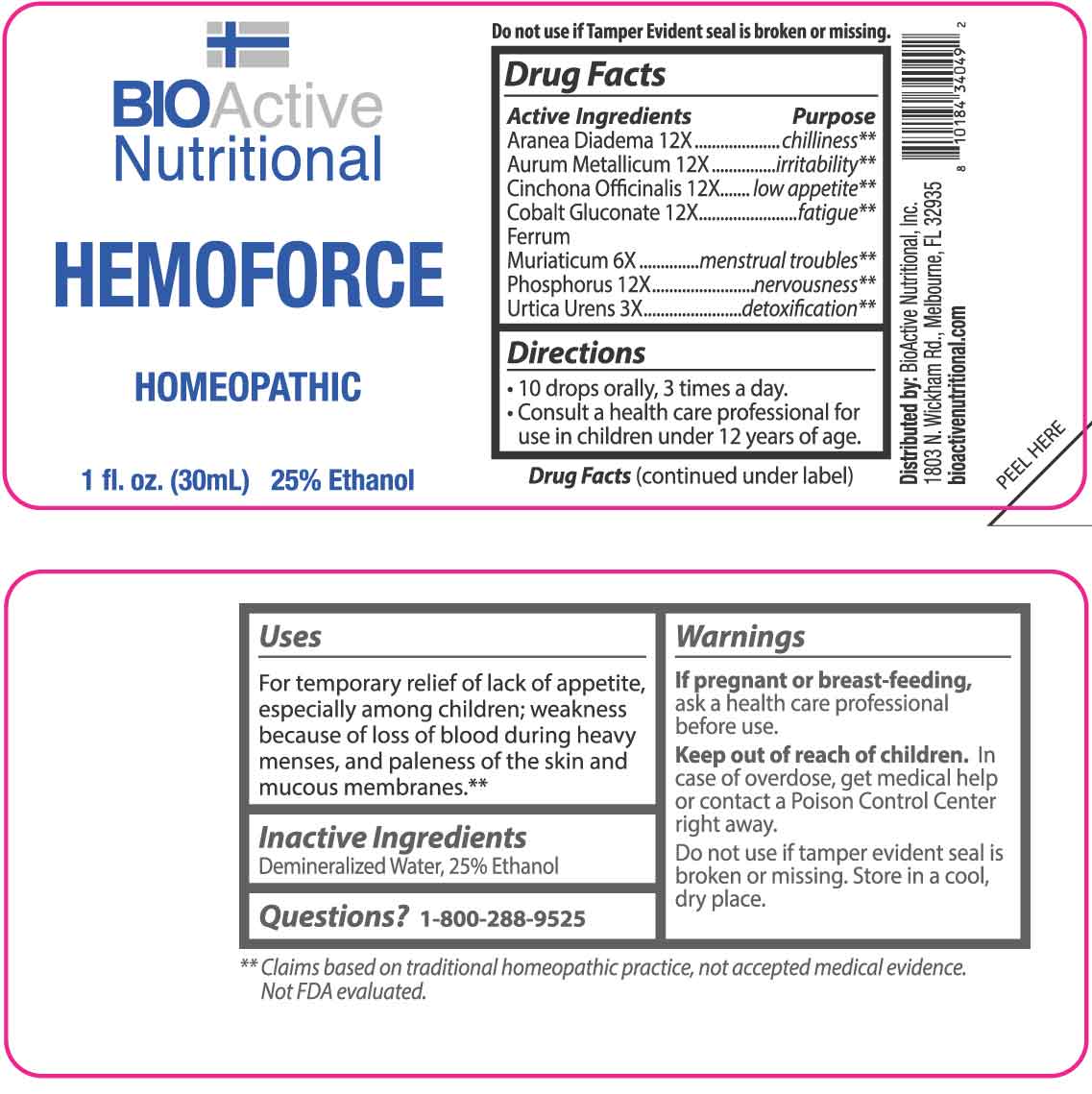 DRUG LABEL: Hemoforce
NDC: 43857-0025 | Form: LIQUID
Manufacturer: BioActive Nutritional, Inc.
Category: homeopathic | Type: HUMAN OTC DRUG LABEL
Date: 20251211

ACTIVE INGREDIENTS: URTICA URENS WHOLE 3 [hp_X]/1 mL; FERRIC CHLORIDE HEXAHYDRATE 6 [hp_X]/1 mL; ARANEUS DIADEMATUS 12 [hp_X]/1 mL; GOLD 12 [hp_X]/1 mL; CINCHONA OFFICINALIS BARK 12 [hp_X]/1 mL; COBALTOUS GLUCONATE 12 [hp_X]/1 mL; PHOSPHORUS 12 [hp_X]/1 mL
INACTIVE INGREDIENTS: WATER; ALCOHOL

DRUG FACTS:

ACTIVE INGREDIENTS:

Aranea Diadema 12X, Aurum Metallicum 12X, Cinchona Officinalis 12X, Cobaltum Gluconate 12X, Ferrum Muriaticum 6X, Phosphorus 12X, Urtica Urens 3X.

PURPOSE:

Aranea Diadema - chilliness,** Aurum Metallicum - irritability,** Cinchona Officinalis – low appetite,** Cobaltum Gluconate - fatigue,** Ferrum Muriaticum – menstrual troubles,** Phosphorus - nervousness,** Urtica Urens – detoxification**

**Claims based on traditional homeopathic practice, not accepted medical evidence. Not FDA evaluated.

USES:

For temporary relief of lack of appetite, especially among children; weakness because of loss of blood during heavy menses, and paleness of the skin and mucous membranes.**

**Claims based on traditional homeopathic practice, not accepted medical evidence. Not FDA evaluated.

WARNINGS:

If pregnant or breast-feeding, ask a health care professional before use.

Keep out of reach of children. In case of overdose, get medical help or contact a Poison Control Center right away.

Do not use if tamper evident seal is broken or missing.

Store in a cool, dry place.

KEEP OUT OF REACH OF CHILDREN

In case of overdose, get medical help or contact a Poison Control Center right away.

DIRECTIONS:

• 10 drops orally, 3 times a day.

• Consult a health care professional for use in children under 12 years of age.

INACTIVE INGREDIENTS:

Demineralized Water, 25% Ethanol

QUESTIONS:

Distributed by:
BioActive Nutritional, Inc.
1803 N. Wickham Rd.
Melbourne, FL 32935
bioactivenutritional.com

1-800-288-9525

PACKAGE LABEL DISPLAY:

BIOActive Nutritional

HEMOFORCE

HOMEOPATHIC

1 fl. oz. (30 mL)